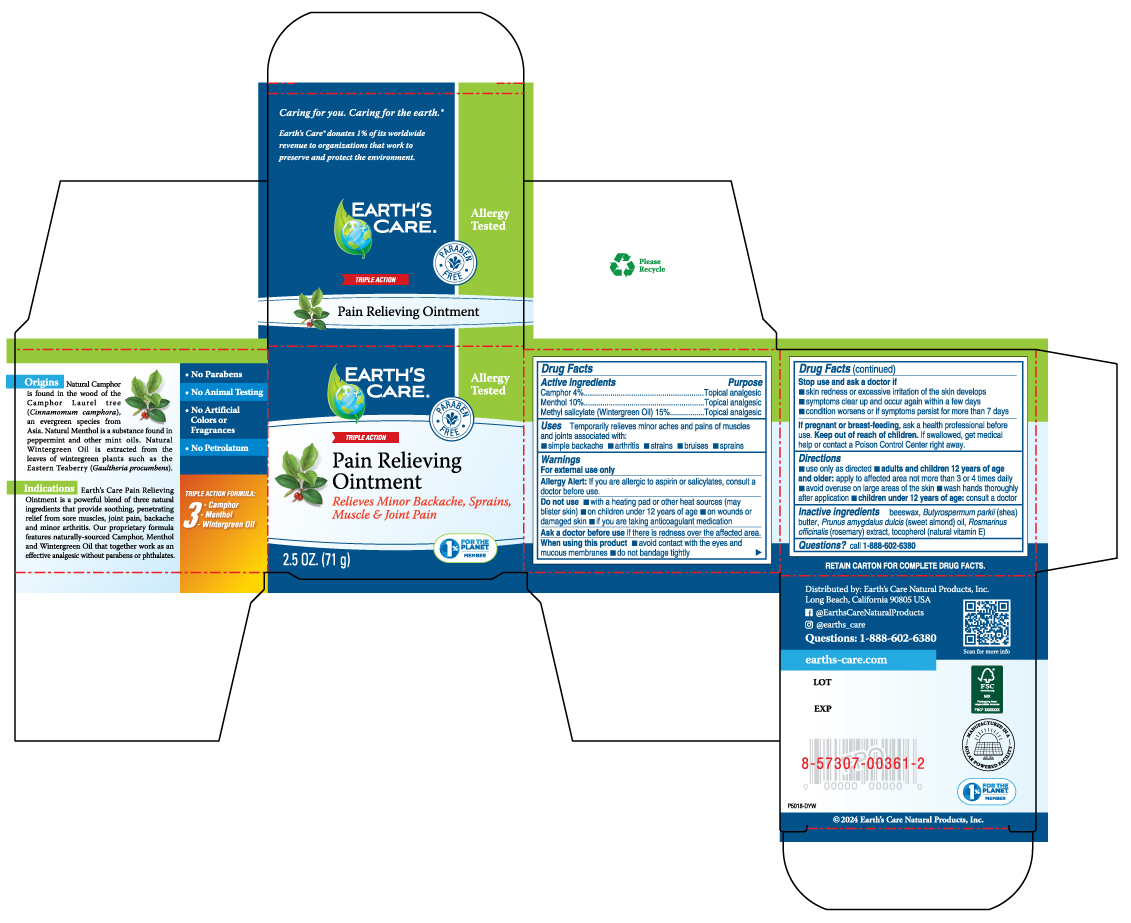 DRUG LABEL: Earths Care Pain Relieving
NDC: 24286-1554 | Form: OINTMENT
Manufacturer: DLC Laboratories, Inc.
Category: otc | Type: HUMAN OTC DRUG LABEL
Date: 20250515

ACTIVE INGREDIENTS: CAMPHOR (NATURAL) 4 g/100 g; MENTHOL, UNSPECIFIED FORM 10 g/100 g; METHYL SALICYLATE 15 g/100 g
INACTIVE INGREDIENTS: YELLOW WAX; ROSEMARY; SHEA BUTTER; ALMOND OIL; TOCOPHEROL

Earth's Care Pain Relieving Ointment

Active Ingredients

Camphor 4%

Menthol 10%

Methyl Salicylate (Wintergreen Oil) 15%

Purpose

Topical Analgesic

Uses

Temporarily relieves the minor aches and pains of muscles and joints associated with:

- simple backache
- arthritis
- strains
- bruises
- sprains

Warnings

For external use only.

Allergy Alert:If you are allergic to aspirin or salicylates, consult a doctor before use.

Do not use

- with a heating pad or other heat sources (may blister skin)
- on children under 12 years of age
- on wounds or damaged skin
- if you are taking anticoagulant medication

Ask a doctor before use

if here is redness over the affected area.

When using this product

- avoid contact with the eyes and mucous membranes
- do not bandage tightly

Stop and ask a doctor if

- skin redness or excessive irritation of the skin develops
- symptoms clear up and occur again within a few days
- condition worsens or if symptoms persist for more than 7 days

Keep out of reach of children.

If swallowed, get medical help or contact a Poison Control Center right away.

If pregnant or breast-feeding,

ask a health professional before use.

Directions

- use only as directed
- adults and children 12 years of age and older: apply to affected area not more than 3 or 4 times daily.
- avoid overuse on large areas of the skin
- wash hands thoroughly after application
- children under 12 years of age: consult a doctor.

Inactive Ingredients

beeswax, Butyrospermum parkii (shea) butter, Prunus amygdalus dulcis (sweet almond) oil, Rosmarinus officinialis (rosemary) extract, tocopherol (natural vitamin E)

Questions?

call 1-888-602-6380

Origins

Natural Camphor is found in the wood of the Camphor Laurel tree (Cinnamomum camphora), an evergreen species from Asia. Natural Menthol is a substance found in peppermint and in other mint oils. Natural Wintergreen Oil is extracted from the leaves of wintergreen plants such as the Eastern Teaberry (Gaultheria procumbens).

Indications

Earth's Care Pain Relieving Ointment is a powerful blend of three natural ingredients that provide soothing, penetrating relief from sore muscles, joint pain, backache and minor arthritis. Our proprietary formula features naturally-sourced Camphor, Menthol and Wintergreen Oil that together work as an effective analgesic without parabens or phthalates.

- No Preservatives
- No Animal Testing
- No Artificial Colors or Fragrances
- No Petrolatum

Triple Action Formula:

- Camphor
- Menthol
- Wintergreen Oil

RETAIN CARTON FOR COMPLETE DRUG FACTS.
Distributed by:
Earth's Care Natural Products, Inc.
Long Beach, California 90805 USA
Questions: 1-888-602-6380
earths-care.com

PRINCIPAL DISPLAY PANEL - 71 g Jar Box

EARTH'S
CARE ®

Allergy
Tested

PARABEN
FREE

TRIPLE ACTION

Pain Relieving
Ointment

Relieves Minor Backache,
Sprains, Muscle & Joint Pain

1%
FOR THE
PLANET
MEMBER

2.5 OZ. (71 g)